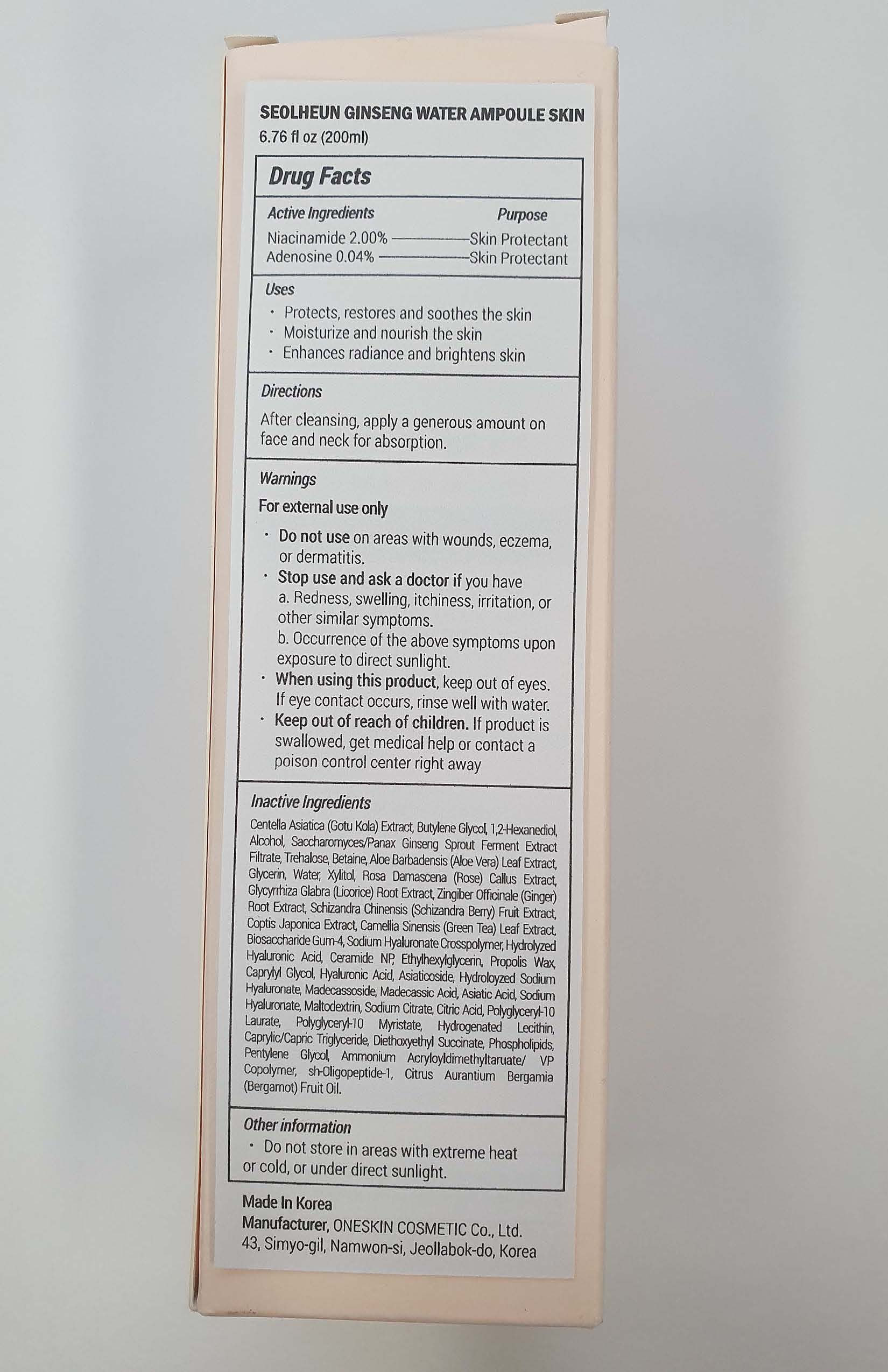 DRUG LABEL: Seolheun Ginseng Water Ampoule Skin
NDC: 70889-510 | Form: LIQUID
Manufacturer: Oneskin Cosmetics Co., Ltd.
Category: otc | Type: HUMAN OTC DRUG LABEL
Date: 20200713

ACTIVE INGREDIENTS: ADENOSINE 0.08 g/200 mL; NIACINAMIDE 4 g/200 mL
INACTIVE INGREDIENTS: BUTYLENE GLYCOL; ASIAN GINSENG; BETAINE; GLYCYRRHIZA GLABRA; SCHISANDRA CHINENSIS FRUIT; CENTELLA ASIATICA

ACTIVE INGREDIENT

Niacinamide 2.00%

Adenosine 0.04%

PURPOSE

Skin Protectant

INDICATIONS AND USAGE

- Protects, restores and soothes the skin
- Moisturize and nourish the skin
- Enhances radiance and brightens skin

DOSAGE AND ADMINISTRATION

After cleansing, apply a generous amount on face and neck for absorption.

WARNINGS

For external use only

- Do not use on areas with wounds, eczema, or dermatitis.
- Stop use and ask a doctor if you have

a. Redness, swelling, itchiness, irritation, or other similar symptoms.
b. Occurrence of the above symptoms upon exposure to direct sunlight.

- When using this product, keep out of eyes. If eye contact occurs, rinse well with water.
- Keep out of reach of children. If product is swallowed, get medical help or contact a poison control center right away

Keep out of reach of children. If product is swallowed, get medical help or contact a poison control center right away

INACTIVE INGREDIENT

Centella Asiatica (Gotu Kola) Extract, Butylene Glycol, 1,2-Hexanediol, Alcohol, Saccharomyces/Panax Ginseng Sprout Ferment Extract Filtrate, Trehalose, Betaine, Aloe Barbadensis (Aloe Vera) Leaf Extract, Glycerin, Water, Xylitol, Rosa Damascena (Rose) Callus Extract, Glycyrrhiza Glabra (Licorice) Root Extract, Zingiber Officinale (Ginger) Root Extract, Schizandra Chinensis (Schizandra Berry) Fruit Extract, Coptis Japonica Extract, Camellia Sinensis (Green Tea) Leaf Extract, Biosaccharide Gum-4, Sodium Hyaluronate Crosspolymer, Hydrolyzed Hyaluronic Acid, Ceramide NP, Ethylhexylglycerin, Propolis Wax, Caprylyl Glycol, Hyaluronic Acid, Asiaticoside, Hydroloyzed Sodium Hyaluronate, Madecassoside, Madecassic Acid, Asiatic Acid, Sodium Hyaluronate, Maltodextrin, Sodium Citrate, Citric Acid, Polyglyceryl-10 Laurate, Polyglyceryl-10 Myristate, Hydrogenated Lecithin, Caprylic/Capric Triglyceride, Diethoxyethyl Succinate, Phospholipids, Pentylene Glycol, Ammonium Acryloyldimethyltaruate/ VP Copolymer, sh-Oligopeptide-1, Citrus Aurantium Bergamia (Bergamot) Fruit Oil.

OTHER SAFETY INFORMATION

- Do not store in areas with extreme heat or cold, or under direct sunlight.